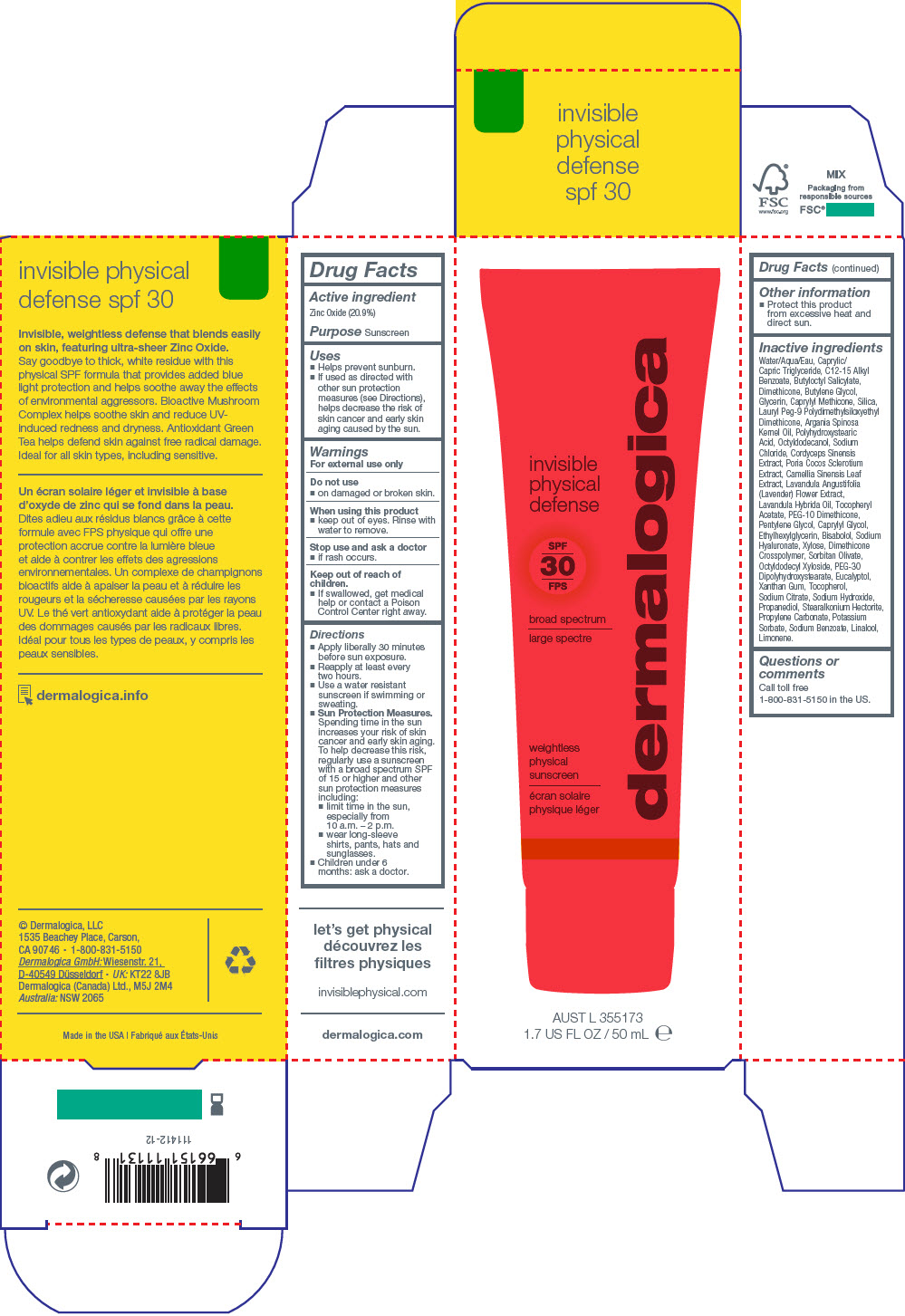 DRUG LABEL: INVISIBLE PHYSICAL DEFENSE SPF30
NDC: 68479-991 | Form: LOTION
Manufacturer: Dermalogica, Inc.
Category: otc | Type: HUMAN OTC DRUG LABEL
Date: 20241227

ACTIVE INGREDIENTS: Zinc Oxide 20.9 mg/1 mL
INACTIVE INGREDIENTS: Water; Medium-Chain Triglycerides; Alkyl (C12-15) Benzoate; Butyloctyl Salicylate; Dimethicone; Butylene Glycol; Glycerin; Caprylyl Trisiloxane; Silicon Dioxide; Lauryl PEG-9 Polydimethylsiloxyethyl Dimethicone; Argan Oil; POLYHYDROXYSTEARIC ACID (2300 MW); Octyldodecanol; Sodium Chloride; Sorbitan Olivate; .Alpha.-Tocopherol Acetate; PEG-10 DIMETHICONE (600 CST); Pentylene Glycol; Propanediol; Octyldodecyl Xyloside; Peg-30 Dipolyhydroxystearate (4000 Mw); Stearalkonium Hectorite; Caprylyl Glycol; Xanthan Gum; Ophiocordyceps Sinensis; FU LING; Sodium Citrate, Unspecified Form; Ethylhexylglycerin; Propylene Carbonate; Lavandin Oil; Levomenol; Hyaluronate Sodium; Green Tea Leaf; Potassium Sorbate; Eucalyptol; Sodium Benzoate; Sodium Hydroxide; Xylose; Lavandula Angustifolia Subsp. Angustifolia Flower; Tocopherol; Linalool, (+/-)-; Limonene, (+)-

INVISIBLE PHYSICAL DEFENSE SPF30

Drug Facts

Active ingredient

Zinc Oxide (20.9%)

Purpose

Sunscreen

Uses

- Helps prevent sunburn.
- If used as directed with other sun protection measures (see Directions), helps decrease the risk of skin cancer and early skin aging caused by the sun.

Warnings

For external use only

Do not use

- on damaged or broken skin.

When using this product

- keep out of eyes. Rinse with water to remove.

Stop use and ask a doctor

- if rash occurs.

Keep out of reach of children.

- If swallowed, get medical help or contact a Poison Control Center right away.

Directions

- Apply liberally 30 minutes before sun exposure.
- Reapply at least every two hours.
- Use a water resistant sunscreen if swimming or sweating.
- Sun Protection Measures. Spending time in the sun increases your risk of skin cancer and early skin aging. To help decrease this risk, regularly use a sunscreen with a broad spectrum SPF of 15 or higher and other sun protection measures including:
  - limit time in the sun, especially from 10 a.m. – 2 p.m.
  - wear long-sleeve shirts, pants, hats and sunglasses.

- Children under 6 months: ask a doctor.

Other information

- Protect this product from excessive heat and direct sun.

Inactive ingredients

Water/Aqua/Eau, Caprylic/Capric Triglyceride, C12-15 Alkyl Benzoate, Butyloctyl Salicylate, Dimethicone, Butylene Glycol, Glycerin, Caprylyl Methicone, Silica, Lauryl Peg-9 Polydimethylsiloxyethyl Dimethicone, Argania Spinosa Kernel Oil, Polyhydroxystearic Acid, Octyldodecanol, Sodium Chloride, Cordyceps Sinensis Extract, Poria Cocos Sclerotium Extract, Camellia Sinensis Leaf Extract, Lavandula Angustifolia (Lavender) Flower Extract, Lavandula Hybrida Oil, Tocopheryl Acetate, PEG-10 Dimethicone, Pentylene Glycol, Caprylyl Glycol, Ethylhexylglycerin, Bisabolol, Sodium Hyaluronate, Xylose, Dimethicone Crosspolymer, Sorbitan Olivate, Octyldodecyl Xyloside, PEG-30 Dipolyhydroxystearate, Eucalyptol, Xanthan Gum, Tocopherol, Sodium Citrate, Sodium Hydroxide, Propanediol, Stearalkonium Hectorite, Propylene Carbonate, Potassium Sorbate, Sodium Benzoate, Linalool, Limonene.

Questions or comments

Call toll free 1-800-831-5150 in the US.

PRINCIPAL DISPLAY PANEL - 50 mL Tube Carton

dermalogica

invisible
physical
defense

SPF
30
FPS

broad spectrum

weightless
physical
sunscreen

Aust L 355173

1.7 US FL OZ / 50 mL e